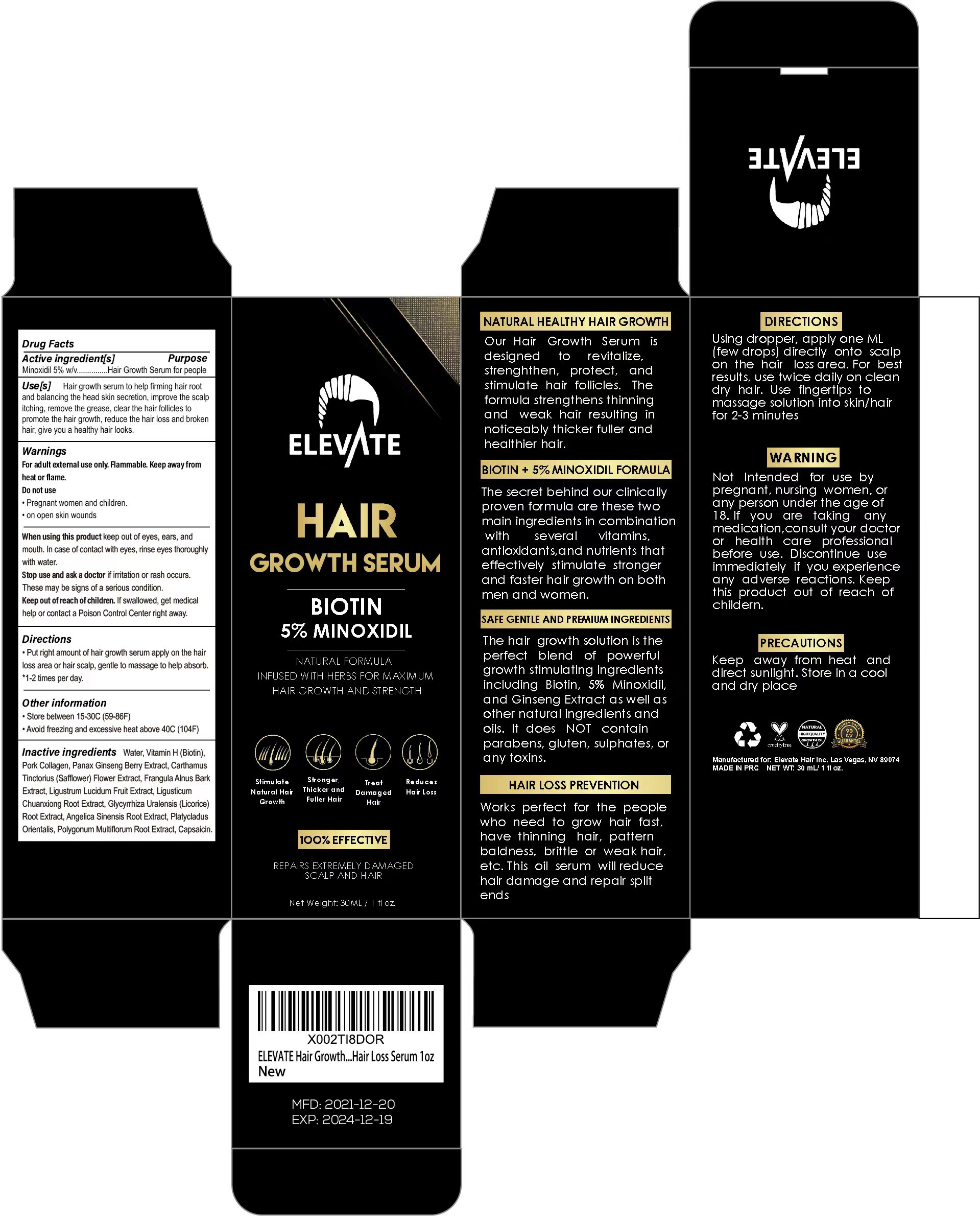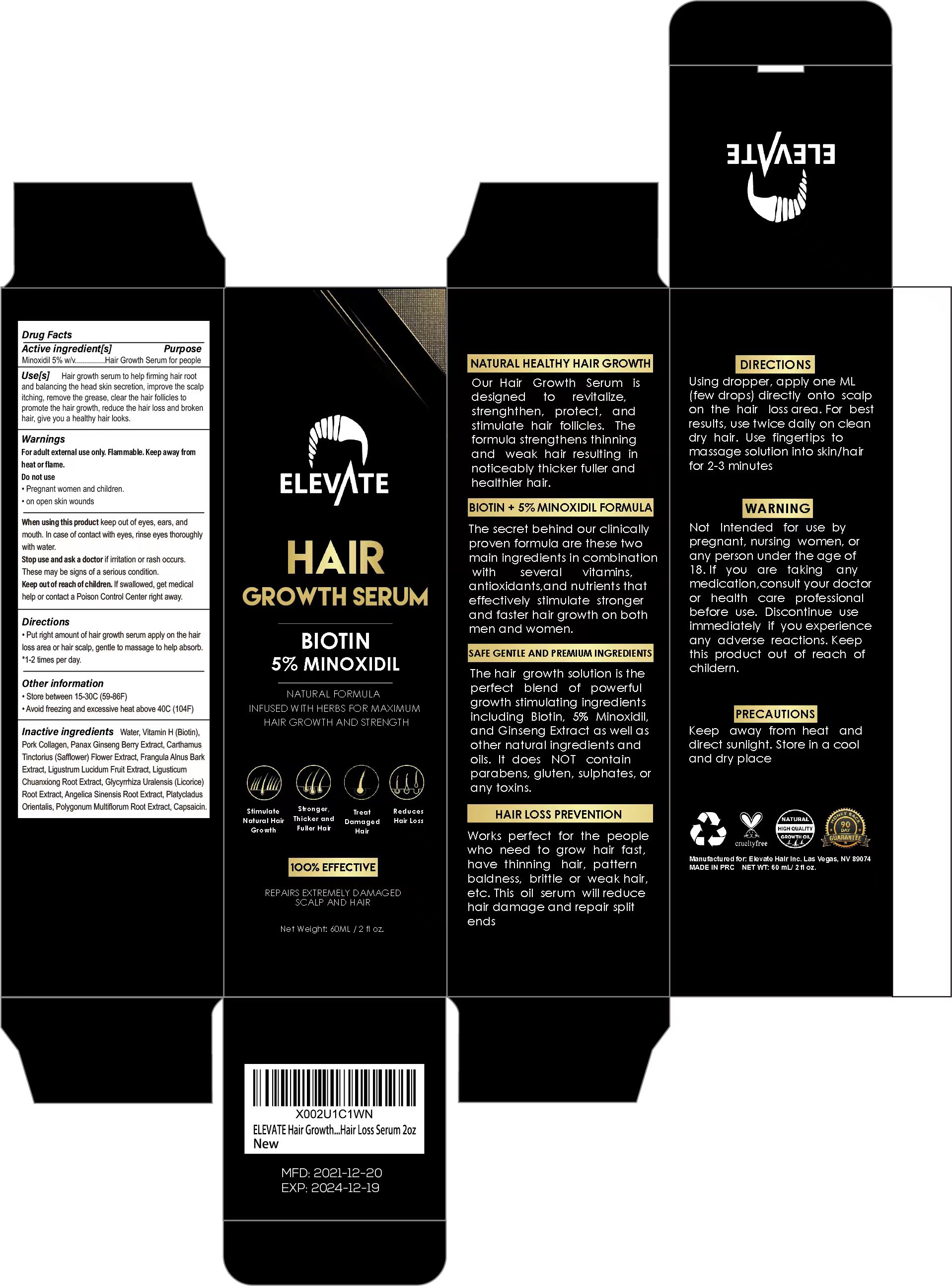 DRUG LABEL: ELEVATE HAIR GROWTH SERUM
NDC: 81653-002 | Form: LIQUID
Manufacturer: Guangzhou Jianyuan Biological Technology.Co.,Ltd
Category: otc | Type: HUMAN OTC DRUG LABEL
Date: 20231219

ACTIVE INGREDIENTS: MINOXIDIL 5 g/100 mL
INACTIVE INGREDIENTS: BIOTIN; GLYCYRRHIZA URALENSIS ROOT; PLATYCLADUS ORIENTALIS WHOLE; REYNOUTRIA MULTIFLORA ROOT; CAPSAICIN; LIGUSTICUM SINENSE SUBSP. CHUANXIONG ROOT; ANGELICA SINENSIS ROOT; WATER; SAFFLOWER; PORK COLLAGEN; PANAX GINSENG FRUIT; LIGUSTRUM LUCIDUM FRUIT

81653-002

Active ingredient

Minoxidil 5% w/v

PURPOSE

Use[s] Hair growth serum to help firming hair rootand balancing the head skin secretion, improve the scalpitching, remove the grease, clear the hair follicles topromote the hair growth, reduce the hair loss and brokenhair, give you a healthy hair looks.

INDICATIONS AND USAGE

Our HairGrowth Serumisdesignedtorevitalize,strenghthen,protect,andstimulate hair follicles. Theformula strengthens thinningandweak hair resulting innoticeably thicker fuller andhealt hier hair.

Works perfect for the people who need to grow hair fast,have thinning hair,patternbaldness,brittle or weak hair ,etc.This oil serum will reducehair damage and repair splitends

Keep out of reach of children.lf swallowed, get medical help or contact a Poison Control Center right away.

WARNINGS

For adult external use only. Flammable. Keep away fromheat or flame.
Do not use
·Pregnant women and children.
·on open skin wounds

When using this product keep out of eyes, ears, andmouth. In case of contact with eyes, rinse eyes thoroughlywith water.
Stop use and ask a doctor if irritation or rash occurs.These may be signs of a serious condition.

ROUTE, METHOD AND FREQUENCY OF ADMINISTRATION

·Put right amount of hair growth serum apply on the hairloss area or hair scalp, gentle to massage to help absorb.
·1-2 times per day.

DOSAGE AND ADMINISTRATION

Using dropper, apply one ML(few drops) directiy 'onto scalpon the hairloss area.For bestresults, use twice daily on cleandry hair. Use fingertips tomassage solution into skin/ hairfor 2-3 minutes

other information

- Store between 15-30℃ (59-86℉)
- Avoid freezing and excessive heat above 40℃ (104℉)

lnactive ingredients

Water, Vitamin H (Biotin), Pork Collagen, Panax Ginseng Berry Extract, CarthamusTinctorius (Safflower) Flower Extract,Frangula Alnus BarkExtract,Ligustrum Lucidum Fruit Extract, LigusticumChuanxiong Root Extract, Glycyrrhiza Uralensis (Licorice)Root Extract, Angelica Sinensis Root Extract, PlatycladusOrientalis,Polygonum Multiflorum Root Extract,Capsaicin.

STOP USE

Not lntendedfor use by pregnant, nursing women, any person under the age of 18. lf you are taking any medication, consult your doctor or health care professional before use. Discontinue use immediately if you experience any adverse reactions. Keep this product out of reach of childern.